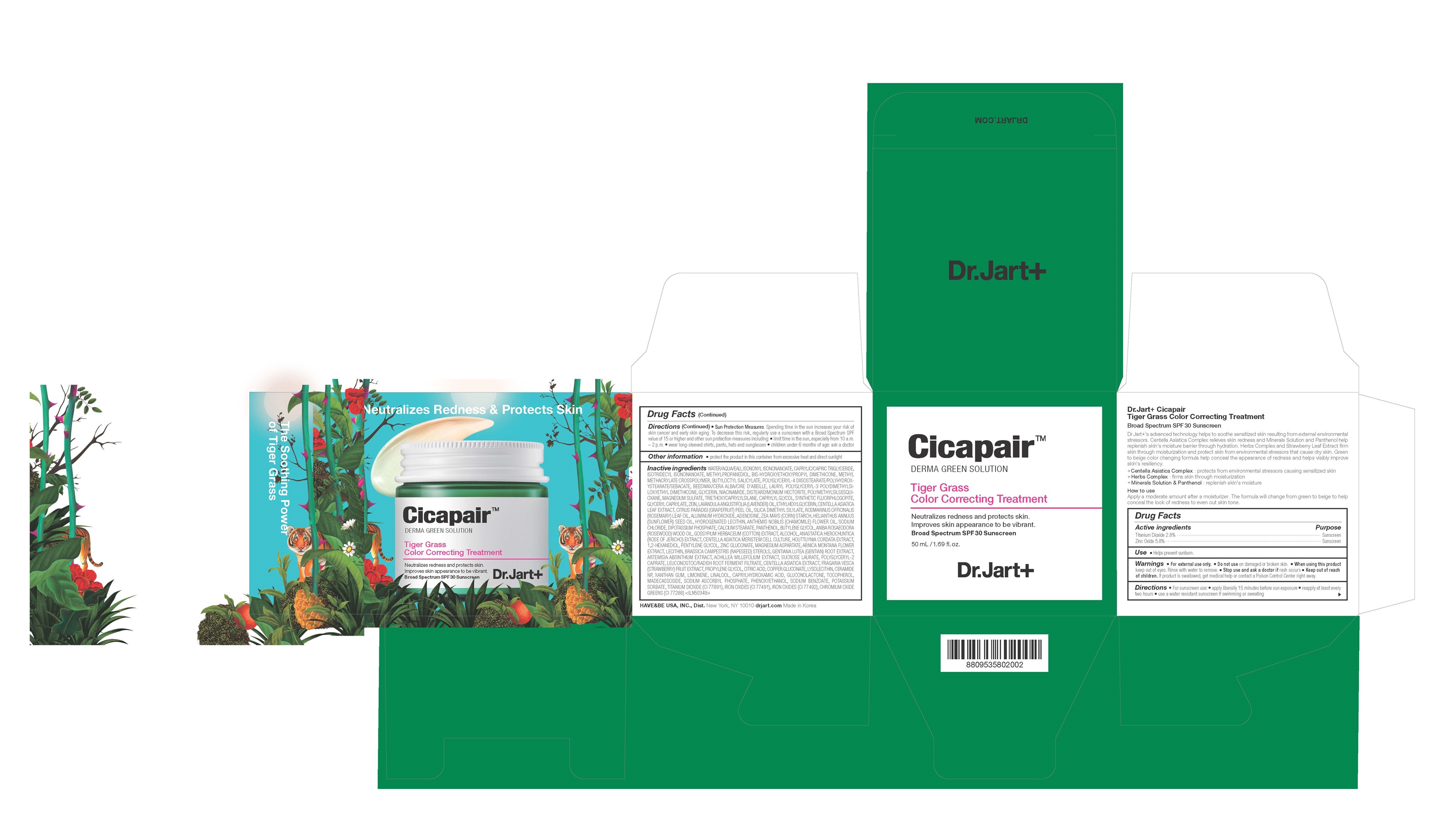 DRUG LABEL: Dr.Jart Cicapair Tiger Grass Color Correcting Treatment
NDC: 49404-147 | Form: CREAM
Manufacturer: Have & Be Co., Ltd.
Category: otc | Type: HUMAN OTC DRUG LABEL
Date: 20241225

ACTIVE INGREDIENTS: ZINC OXIDE 5.8 g/100 mL; TITANIUM DIOXIDE 2.8 g/100 mL
INACTIVE INGREDIENTS: WATER; ISONONYL ISONONANOATE; MEDIUM-CHAIN TRIGLYCERIDES; ISOTRIDECYL ISONONANOATE; METHYLPROPANEDIOL; BIS-HYDROXYETHOXYPROPYL DIMETHICONE (37 CST); METHYL METHACRYLATE/GLYCOL DIMETHACRYLATE CROSSPOLYMER; BUTYLOCTYL SALICYLATE; YELLOW WAX; GLYCERIN; NIACINAMIDE; DISTEARDIMONIUM HECTORITE; MAGNESIUM SULFATE, UNSPECIFIED FORM; POLYMETHYLSILSESQUIOXANE (4.5 MICRONS); FERRIC OXIDE RED; TRIETHOXYCAPRYLYLSILANE; CAPRYLYL GLYCOL; CHROMIC OXIDE; FERRIC OXIDE YELLOW; GLYCERYL MONOCAPRYLATE; ZEIN; LAVENDER OIL; ETHYLHEXYLGLYCERIN; CENTELLA ASIATICA LEAF; GRAPEFRUIT OIL; SILICA DIMETHYL SILYLATE; ROSEMARY OIL; ALUMINUM HYDROXIDE; ADENOSINE; STARCH, CORN; SUNFLOWER OIL; HYDROGENATED SOYBEAN LECITHIN; CAPRYLHYDROXAMIC ACID; CHAMAEMELUM NOBILE FLOWER OIL; TOCOPHEROL; CALCIUM STEARATE; MADECASSOSIDE; SODIUM CHLORIDE; PANTHENOL; BUTYLENE GLYCOL; ROSEWOOD OIL; LEVANT COTTON SEED; ALCOHOL; ANASTATICA HIEROCHUNTICA WHOLE; HOUTTUYNIA CORDATA FLOWERING TOP; 1,2-HEXANEDIOL; PENTYLENE GLYCOL; MAGNESIUM ASPARTATE; ZINC GLUCONATE; ARNICA MONTANA FLOWER; RAPESEED STEROL; ACHILLEA MILLEFOLIUM WHOLE; GENTIANA LUTEA ROOT; WORMWOOD; LEUCONOSTOC/RADISH ROOT FERMENT FILTRATE; POLYGLYCERYL-2 CAPRATE; SUCROSE LAURATE; CENTELLA ASIATICA WHOLE; FRAGARIA VESCA FRUIT; PHENOXYETHANOL; PROPYLENE GLYCOL; GLUCONOLACTONE; COPPER GLUCONATE; CERAMIDE NP; LYSOPHOSPHATIDYLCHOLINE, SOYBEAN; CITRIC ACID MONOHYDRATE; XANTHAN GUM; SODIUM ASCORBYL PHOSPHATE; SODIUM BENZOATE; POTASSIUM SORBATE; LIMONENE, (+)-; LINALOOL, (+/-)-

Dr.Jart Cicapair Tiger Grass Color Correcting Treatment

ACTIVE INGREDIENT

Zinc Oxide 5.8%

Titanium Dioxide 2.8%

PURPOSE

Sunscreen

INDICATIONS AND USAGE

Helps prevent sunburn

DOSAGE AND ADMINISTRATION

- For Sunscreen use: Apply liberally 15 minutes before sun exposure.
- Reapply at least every 2 hours.
- Use a water resistant sunscreen if swimming or sweating
- Sun Protection Measures. Spending time in the sun increases your risk of skin cancer and early skin aging. To decrease this risk, regularly use a sunscreen with a Broad Spectrum SPF value of 15 or higher and other sun protection measures including:

– Limit time in the sun, especially from 10 am - 2 pm

- Wear long-sleeved shirts, pants, hats and sunglasses

- Children under 6 months: Ask a doctor

WARNINGS

For external use only.

Do not use on damaged or broken skin.

When using this product, keep out of eyes. Rinse with water to remove.

Stop use and ask a doctor if rash occurs.

KEEP OUT OF REACH OF CHILDREN

Keep out of reach of the children. If product is swallowed, get medical help or contact a poison control center right away.

INACTIVE INGREDIENT

WATER/AQUA/EAU, ISONONYL ISONONANOATE, CAPRYLIC/CAPRIC TRIGLYCERIDE, ISOTRIDECYL ISONONANOATE, TITANIUM DIOXIDE(CI 77891), METHYLPROPANEDIOL, BIS-HYDROXYETHOXYPROPYL DIMETHICONE, METHYL METHACRYLATE CROSSPOLYMER, BUTYLOCTYL SALICYLATE, POLYGLYCERYL-4 DIISOSTEARATE/POLYHYDROXYSTEARATE/SEBACATE, BEESWAX/CERA ALBA/CIRE D'ABEILLE, LAURYL POLYGLYCERYL-3 POLYDIMETHYLSILOXYETHYL DIMETHICONE, GLYCERIN, NIACINAMIDE, DISTEARDIMONIUM HECTORITE, POLYMETHYLSILSESQUIOXANE, MAGNESIUM SULFATE, IRON OXIDES(CI 77492), TRIETHOXYCAPRYLYLSILANE, CAPRYLYL GLYCOL, CHROMIUM OXIDE GREENS, SYNTHETIC FLUORPHLOGOPITE, IRON OXIDES(CI 77491), GLYCERYL CAPRYLATE, ZEIN, LAVANDULA ANGUSTIFOLIA (LAVENDER) OIL, ETHYLHEXYLGLYCERIN, CENTELLA ASIATICA LEAF EXTRACT, CITRUS PARADISI (GRAPEFRUIT) PEEL OIL, SILICA DIMETHYL SILYLATE, ROSMARINUS OFFICINALIS (ROSEMARY) LEAF OIL, ALUMINUM HYDROXIDE, ADENOSINE, ZEA MAYS (CORN) STARCH, HELIANTHUS ANNUUS (SUNFLOWER) SEED OIL, HYDROGENATED LECITHIN, CAPRYLHYDROXAMIC ACID, ANTHEMIS NOBILIS FLOWER OIL, TOCOPHEROL, CALCIUM STEARATE, DIPOTASSIUM PHOSPHATE, MADECASSOSIDE, SODIUM CHLORIDE, PANTHENOL, BUTYLENE GLYCOL, ANIBA ROSODORA (ROSEWOOD) WOOD OIL, GOSSYPIUM HERBACEUM (COTTON) EXTRACT, ALCOHOL, ANASTATICA HIEROCHUNTICA EXTRACT, CENTELLA ASIATICA MERISTEM CELL CULTURE, HOUTTUYNIA CORDATA EXTRACT, 1,2-HEXANEDIOL, PENTYLENE GLYCOL, MAGNESIUM ASPARTATE, ZINC GLUCONATE, ARNICA MONTANA FLOWER EXTRACT, LECITHIN, BRASSICA CAMPESTRIS (RAPESEED) STEROLS, ACHILLEA MILLEFOLIUM EXTRACT, GENTIANA LUTEA ROOT EXTRACT, ARTEMISIA ABSINTHIUM EXTRACT, LEUCONOSTOC/RADISH ROOT FERMENT FILTRATE, POLYGLYCERYL-2 CAPRATE, SUCROSE LAURATE, CENTELLA ASIATICA EXTRACT, FRAGARIA VESCA (STRAWBERRY) FRUIT EXTRACT, PHENOXYETHANOL, PROPYLENE GLYCOL, GLUCONOLACTONE, COPPER GLUCONATE, CERAMIDE NP, LYSOLECITHIN, CITRIC ACID, XANTHAN GUM, SODIUM ASCORBYL PHOSPHATE, SODIUM BENZOATE, POTASSIUM SORBATE, LIMONENE, LINALOOL

STORAGE AND HANDLING

Protect the product in this container from excessive heat and direct sunlight

PACKAGE LABEL

Cicapair
DERMA GRENN SOLUTION
Tiger Grass Color Correcting Treatment

Neutralizes redness and protects skin.

Improves skin apperance to be vibrant.

Broad Spectrum SPF30 Sunscreen

50mL / 1.69 fl.oz

Dr. Jart +